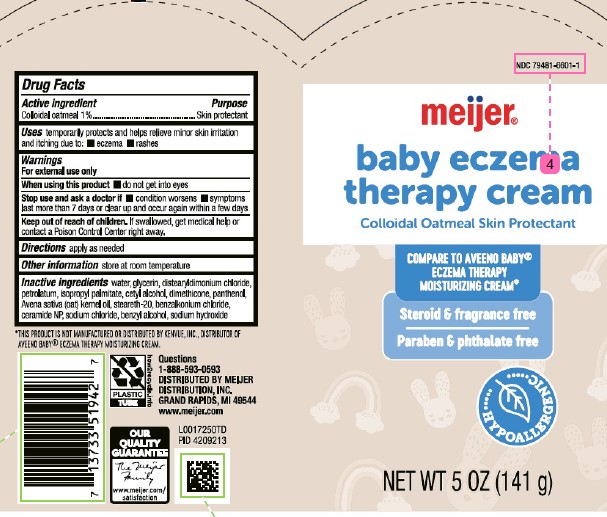 DRUG LABEL: Colloidal oatmeal
NDC: 79481-6601 | Form: CREAM
Manufacturer: Meijer, Inc.
Category: otc | Type: HUMAN OTC DRUG LABEL
Date: 20260219

ACTIVE INGREDIENTS: OATMEAL 10 mg/1 g
INACTIVE INGREDIENTS: GLYCERIN; DISTEARYLDIMONIUM CHLORIDE; PETROLATUM; ISOPROPYL PALMITATE; CETYL ALCOHOL; DIMETHICONE; PANTHENOL; OAT KERNEL OIL; STEARETH-20; BENZALKONIUM CHLORIDE; CERAMIDE 3; SODIUM CHLORIDE; BENZYL ALCOHOL; SODIUM HYDROXIDE; WATER

Meijer 601.001/601AB
Eczema Soothing Moisturizing Cream

Active ingredient

Colloidal oatmeal 1%

Purpose

Skin protectant

Uses

temporarily protects and helps relieve minor skin irritation and itching due to:

- eczema
- rashes

Warnings

For external use only

When using this product

- do not get into eyes

Stop use and ask a doctor if

- condition worsens
- symptoms last more than 7 days or clear up and occur again withing a few days

Keep out of reach of children.

If swallowed, get medical help or contact a Poison Control Center right away.

Directions

apply as needed

Other information

store at room temperature

Inactive ingredients

water, glycerin, distearyldimonium chloride, petrolatum, isopropyl palmitate, cetyl alcohol, dimethicone, pathenol, Avena sativa (oat) kernel oil, steareth-20, benzalkonium chloride, ceramide NP, sodium chloride, benzyl alcohol, sodium hydroxide

Disclaimer

*This product is not manufactured or distributed by Kenvue, Inc., distributor of Aveeno BabyEczema Therapy Moisturizing Cream.

Adverse reaction

Questions

1-888-593-0593

DISTRIBUTED BY

MEIJER DISTRIBUTION, INC.,

GRAND RAPIDS, MI 49544

www.meijer.com

PLASTIC TUBE

how2recycle.info

OUR QUALITY GUARANTEE

The Meijer Family

www.meijer.com/satisfaction

Principal Panel Display

NDC 79481-6601-1

meijer®

baby eczema

therapy cream

Colloidal Oatmeal Skin Protectant

COMPARE TO AVEENO®BABY ECZEMA THERAPY MOISTURIZING CREAM*

Steroid & fragrance free

Paraben & phthalate free

HYPOALLERGENIC

NET WT. 5 OZ (141 g)